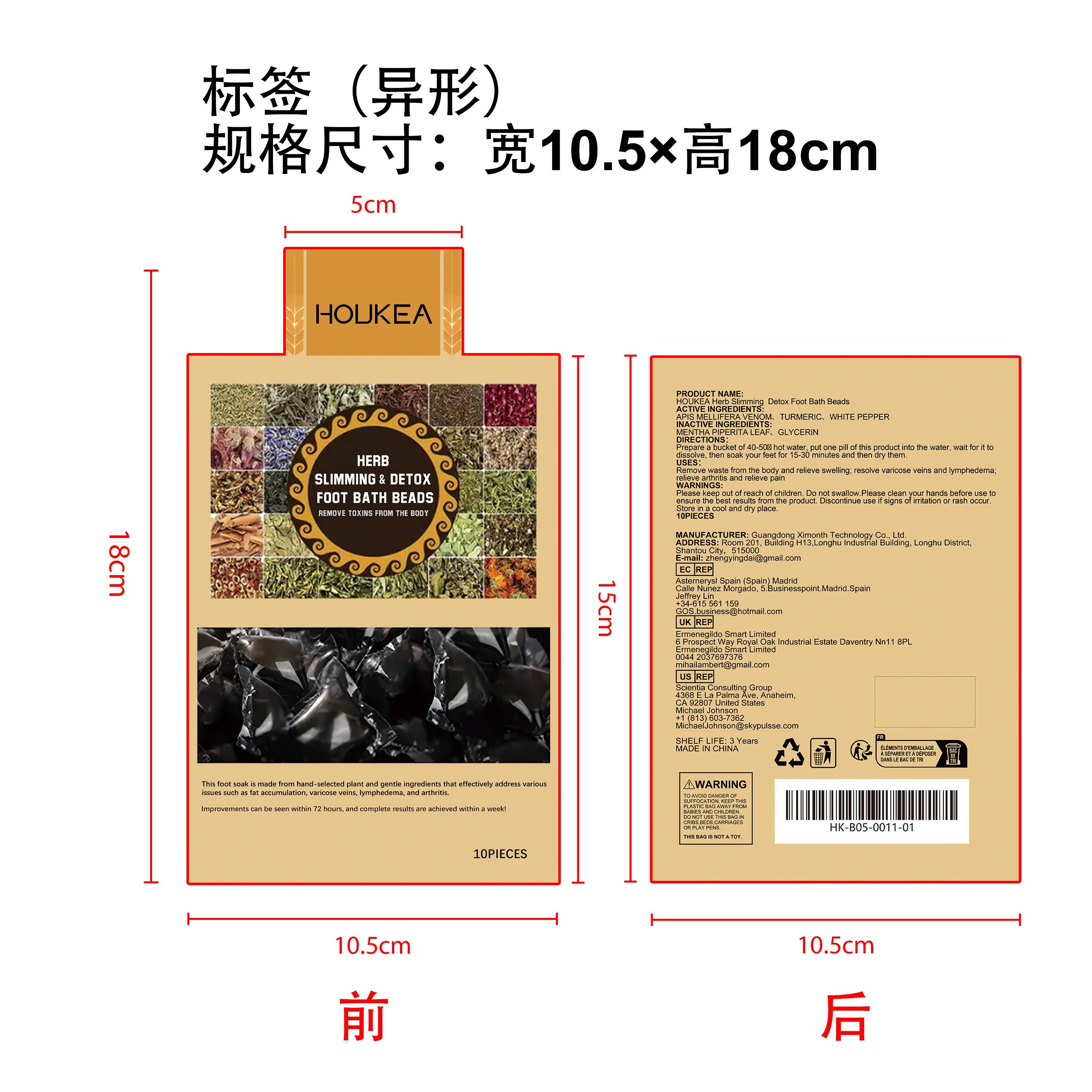 DRUG LABEL: HOUKEA Herb Slimming Detox Foot Bath Beads
NDC: 84660-083 | Form: LIQUID
Manufacturer: Guangdong Ximonth Technology Co., Ltd.
Category: otc | Type: HUMAN OTC DRUG LABEL
Date: 20241021

ACTIVE INGREDIENTS: APIS MELLIFERA VENOM 2.5 g/10 g; WHITE PEPPER 1 g/10 g; TURMERIC 1 g/10 g
INACTIVE INGREDIENTS: GLYCERIN 3 g/10 g; MENTHA PIPERITA LEAF 2.5 g/10 g

Active Ingredient(s)

APIS MELLIFERA VENOM、TURMERIC、 WHITE PEPPER

Purpose

Remove waste from the body and relieve swelling; resolve varicose veins and lymphedema; relieve arthritis and relieve páin

Use

Prepare a bucket of 40-50℃ hot water, put one pill of this product into the water, wait for it toldissolve, then soak your feet for 15-30 minutes and then dry them.

Warnings

Please keep out of reach of children.Do not swallow.Please clean your hands before use to ensure the best results from the product.Discontinue use if signs of irritation or rash occur.Store in a cool and dry place.

Do not use

Discontinue use if signs of irritation or rash occur.

STOP USE

Discontinue use if signs of irritation or rash occur.

KEEP OUT OF REACH OF CHILDREN

Please keep out of reach of children. Do not swallow.

STORAGE AND HANDLING

Store in a cool and dry place.

INACTIVE INGREDIENT

MENTHA PIPERITA LEAF、GLYCERIN